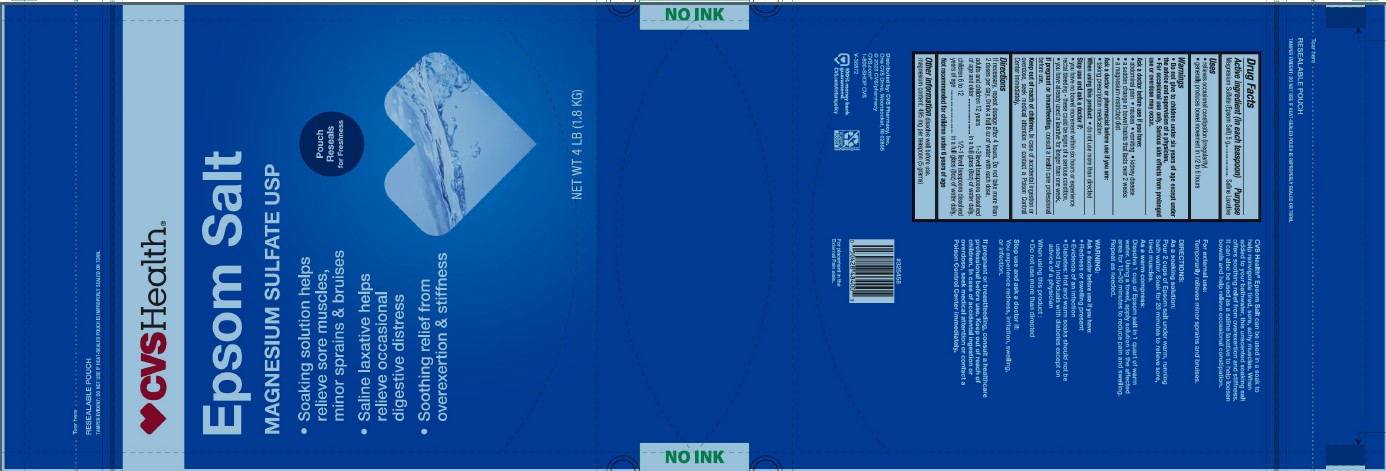 DRUG LABEL: Epsom Salt
NDC: 51316-072 | Form: GRANULE
Manufacturer: CVS PHARMACY
Category: otc | Type: HUMAN OTC DRUG LABEL
Date: 20250320

ACTIVE INGREDIENTS: MAGNESIUM SULFATE HEPTAHYDRATE 1 g/1 g

CVS Health Epsom Salt

Active ingredient (in each teaspoon)

Magnesium Sulfate (Epsom Salt) 5 g

Purpose

External Use ...................................................... Soaking Solution
Internal Use .......................................................... Saline Laxative

Uses

External

• temporarily relieves minor sprains and bruises

Internal

• relieves occasional constipation (irregularity)
• generally produces bowel movement in 1/2 to 6 hours

Warnings

As a laxative • Do not give to children under six years of age except under the advice and supervision of a physician.

• For occasional use only. Serious side effects from prolonged use or overdose may occur.

Ask a doctor before use if you have:

As a soaking solution

- redness or swelling present

• evidence of an infection

• diabetes - hot and warm soaks should not be used by individuals with diabetes except on advice of a physician

As a laxative
• abdominal pain

- nausea
- vomiting
- kidney disease
- a sudden change in bowel habits that lasts over 2 weeks
- a magnesium-restricted diet

Ask a doctor or pharmacist before use if you are:

As a laxative • taking prescription medication

When using this product

• do not use more than directed

Stop use and ask a doctor if:

As a soaking solution
• you experience redness, irritation, swelling or infection.

As a laxative
• you have no bowel movement within six hours or experience rectal bleeding - these could be signs of a serious condition.
• you have already used a laxative for longer than one week.

If pregnant or breastfeeding

consult a health care professional before use.

Keep out of reach of children.

In case of accidental ingestion or overdose, seek medical attention or contact a Poison Control Center immediately.

Directions

As a soaking solution: Pour 2 cups of Epsom Salt under warm, running bath water. Soak for 20 minutes to relieve sore, tired muscles.
As a warm compress: Dissolve 1 cup of Epsom Salt in 1 quart of warm water. Using a towel, apply solution to the affected area for 15-30 minutes to reduce pain and swelling. Repeat as needed.
As a laxative: If necessary, repeat dosage after 4 hours. Do not take more than 2 doses per day. Drink a full 8 oz of water with each dose.

adults and children 12 years of age and older .......................1-3 level teaspoons dissolved in a full glass (8oz) of water daily.
children 6 to 12years of age ............................1/2-1 level teaspoons dissolved in a full glass (8oz) of water daily.

Not recommended for children under 6 years of age

Other information

dissolve well before use.
magnesium content: 495 mg per teaspoon (5 grams)

Inactive ingredient

None